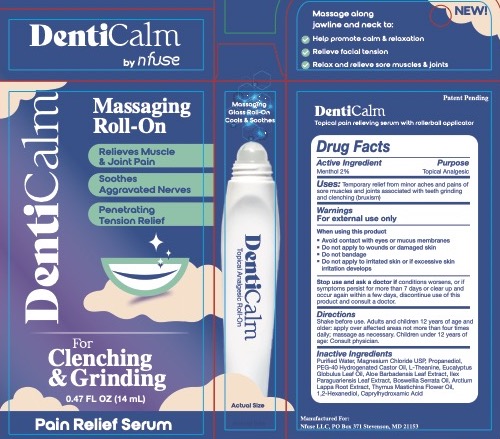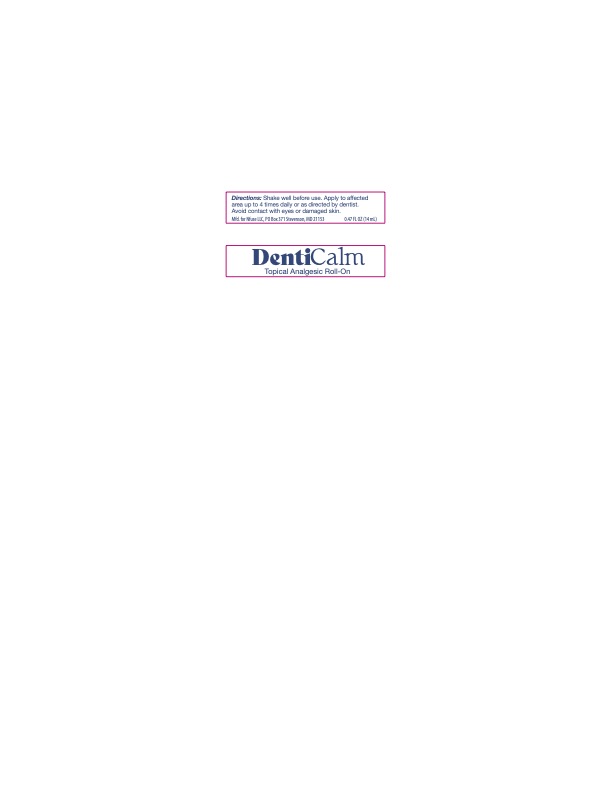 DRUG LABEL: DentiCalm
NDC: 82765-0002 | Form: EMULSION
Manufacturer: NFUSE LLC
Category: otc | Type: HUMAN OTC DRUG LABEL
Date: 20251016

ACTIVE INGREDIENTS: MENTHOL 2 g/1 mL
INACTIVE INGREDIENTS: WATER; MAGNESIUM CHLORIDE; PROPANEDIOL; PEG-40 CASTOR OIL; THEANINE; EUCALYPTUS GLOBULUS LEAF; ALOE VERA LEAF; ILEX PARAGUARIENSIS LEAF; BOSWELLIA SERRATA WHOLE; ARCTIUM LAPPA ROOT OIL; THYMUS MASTICHINA FLOWERING TOP OIL; 1,2-HEXANEDIOL; CAPRYLHYDROXAMIC ACID

DentiCalm Massaging Roll On

Active Ingredient

Menthol 2% Purpose: Topical Analgesic

Usage

Temporary relief from minor aches and pains of sore muscles and joints associated with teeth grinding and clenching (bruxism)

Warnings

For External Use Only
When using this product:
[bullet] Avoid contact with eyes and mucous membranes
[bullet] Do not apply to wounds or broken skin
[bullet] Do not bandage
[bullet] Do not apply to irritated skin or if excessive skin irritation develops
Stop use and ask a doctor if conditions worsens, or if symptoms persist for more than 7 days or clear up and occur again within a few days, discontinue use of this product and consult a doctor.

Keep out of reach of children.

Directions

Shake before use. Adults and children 12 years of age and older: apply over affected areas not more than four times daily; massage as necessary. Children under 12 years of age: Consult physician.

Inactive Ingredients

Water, Magnesium Chloride USP, Propanediol, PEG-40 Hydrogenated Castor Oil, L-Theanine, Eucalyptus Globulus Leaf Oil, Aloe Barbadensis Leaf Extract, Ilex Paraguariensis Leaf Extract, Boswellia Serrata Oil, Arctium Lappa Root Extract, Thymus Mastichina Flower Oil, 1,2-Hexanediol, Caprylhydroxamic Acid

Purpose

Purpose: Topical Analgesic

Dosage & Admnistration

Shake before use. Adults and children 12 years of age and older: apply over affected areas not more than four times daily; massage as necessary. Children under 12 years of age: Consult physician.

Outer Package

NDC 82765-0002-0

Inner Primary Container Label Front and Back

NDC 82765-0002-1